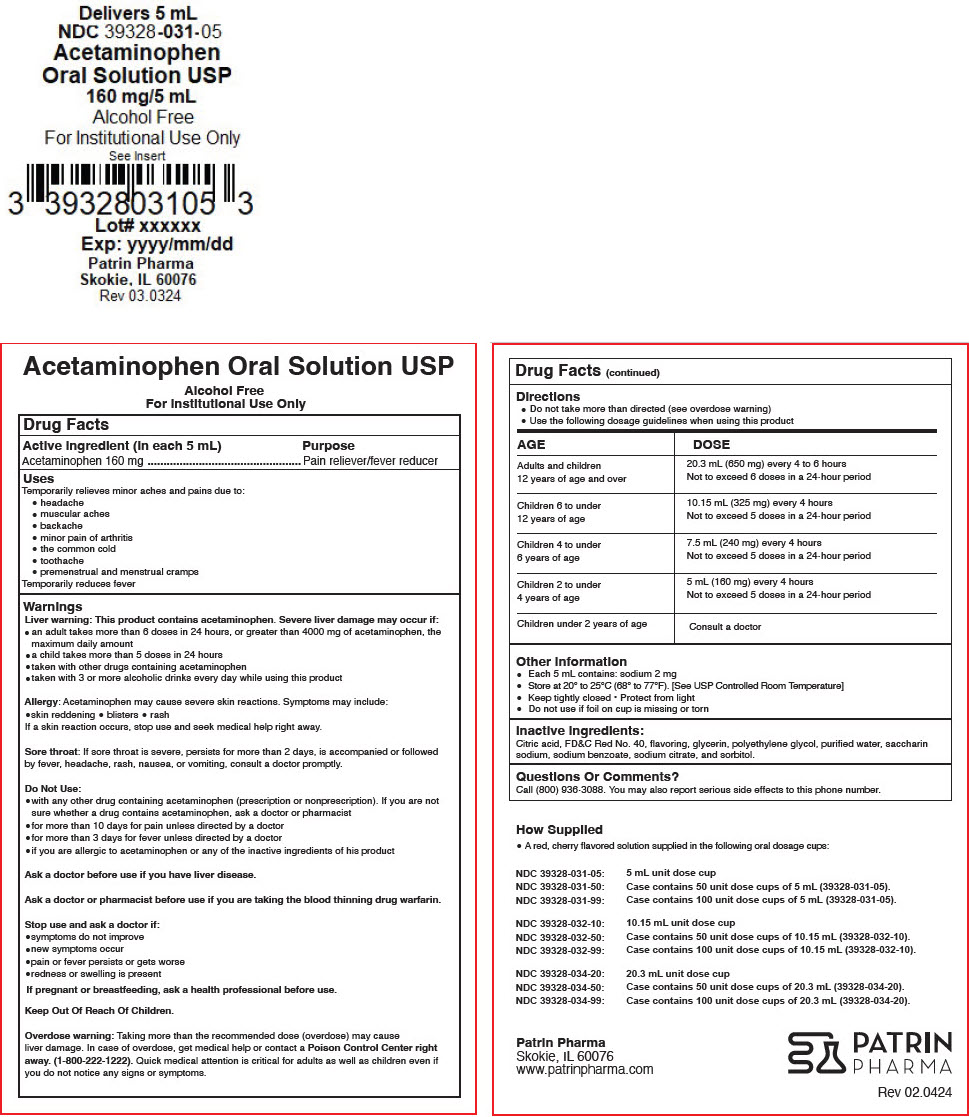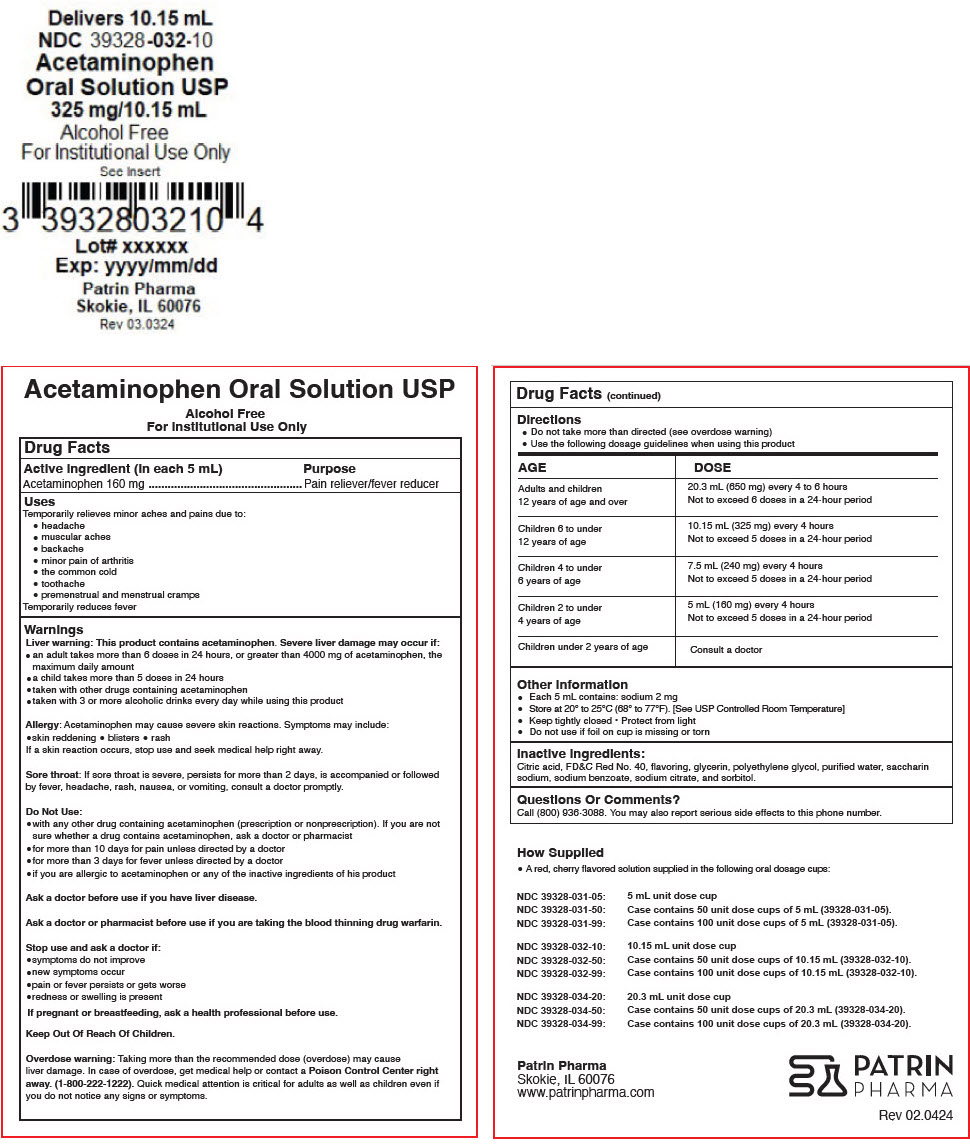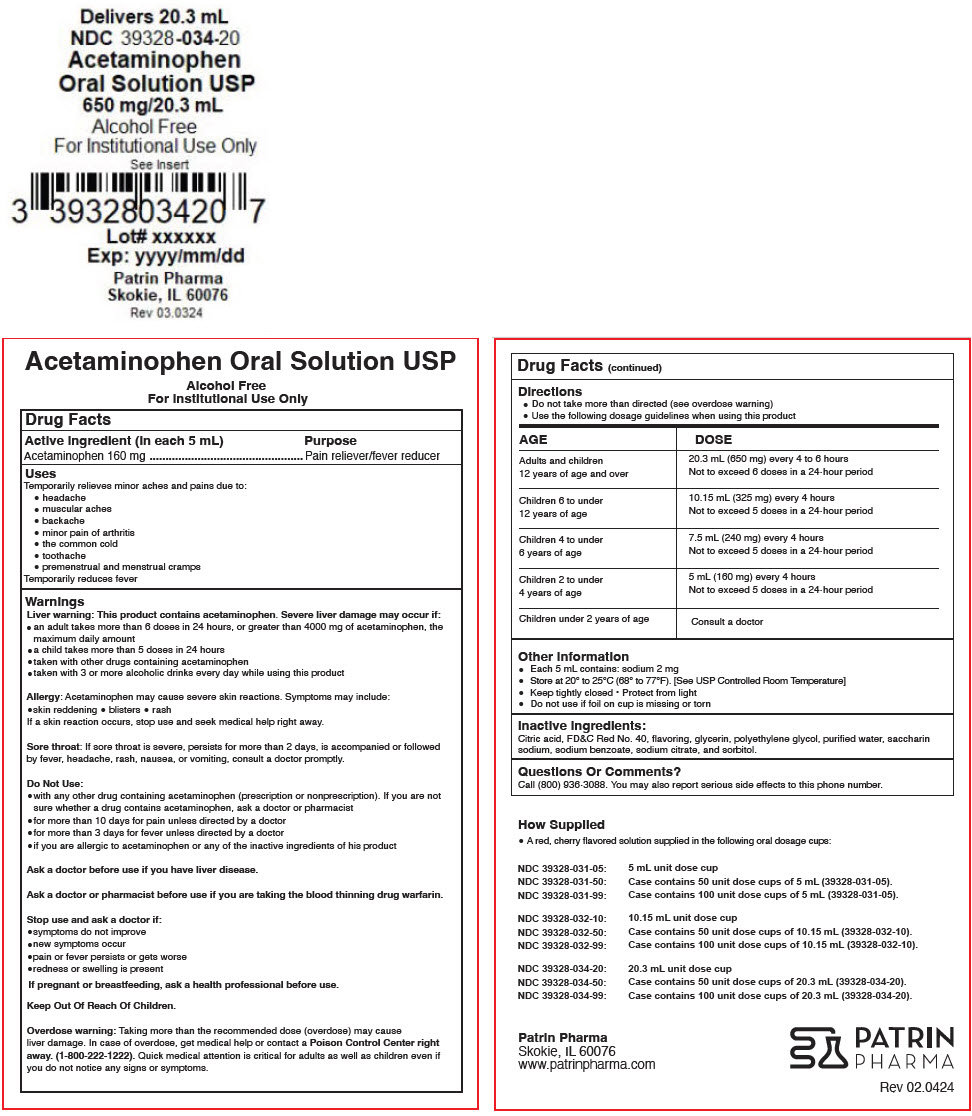 DRUG LABEL: Acetaminophen Solution
NDC: 39328-031 | Form: LIQUID
Manufacturer: Patrin Pharma, Inc.
Category: otc | Type: HUMAN OTC DRUG LABEL
Date: 20240521

ACTIVE INGREDIENTS: Acetaminophen 160 mg/5 mL
INACTIVE INGREDIENTS: ANHYDROUS CITRIC ACID; FD&C RED NO. 40; Glycerin; POLYETHYLENE GLYCOL 400; WATER; Saccharin sodium; Sodium benzoate; SODIUM CITRATE, UNSPECIFIED FORM; Sorbitol

Acetaminophen Oral Solution USP UD

Drug Facts

Active ingredient (in each 5 mL)

Acetaminophen 160 mg

Purpose

Pain reliever/fever reducer

Uses

Temporarily relieves minor aches and pains due to:

- headache
- muscular aches
- backache
- minor pain of arthritis
- the common cold
- toothache
- premenstrual and menstrual cramps

Temporarily reduces fever

Warnings

Liver warning

This product contains acetaminophen. Severe liver damage may occur if:

- an adult takes more than 6 doses in 24 hours, or greater than 4000 mg of acetaminophen, the maximum daily amount
- a child takes more than 5 doses in 24 hours
- taken with other drugs containing acetaminophen
- taken with 3 or more alcoholic drinks every day while using this product

Allergy

Acetaminophen may cause severe skin reactions. Symptoms may include:

- skin reddening
- blisters
- rash

If a skin reaction occurs, stop use and seek medical help right away.

Sore throat

If sore throat is severe, persists for more than 2 days, is accompanied or followed by fever, headache, rash, nausea, or vomiting, consult a doctor promptly.

Do Not Use

- with any other drug containing acetaminophen (prescription or nonprescription). If you are not sure whether a drug contains acetaminophen, ask a doctor or pharmacist
- for more than 10 days for pain unless directed by a doctor
- for more than 3 days for fever unless directed by a doctor
- if you are allergic to acetaminophen or any of the inactive ingredients of his product

Ask a doctor before use if you have liver disease.

Ask a doctor or pharmacist before use if you are taking the blood thinning drug warfarin.

Stop use and ask a doctor if

- symptoms do not improve
- new symptoms occur
- pain or fever persists or gets worse
- redness or swelling is present

PREGNANCY OR BREAST FEEDING

If pregnant or breastfeeding, ask a health professional before use.

Keep Out Of Reach Of Children.

Overdose warning

Taking more than the recommended dose (overdose) may cause liver damage. In case of overdose, get medical help or contact a Poison Control Center right away. (1-800-222-1222). Quick medical attention is critical for adults as well as children even if you do not notice any signs or symptoms.

Directions

- Do not take more than directed (see overdose warning)
- Use the following dosage guidelines when using this product

AGE | DOSE
Adults and children 12 years of age and over | 20.3 mL (650 mg) every 4 to 6 hours Not to exceed 6 doses in a 24-hour period
Children 6 to under 12 years of age | 10.15 mL (325 mg) every 4 hours Not to exceed 5 doses in a 24-hour period
Children 4 to under 6 years of age | 7.5 mL (240 mg) every 4 hours Not to exceed 5 doses in a 24-hour period
Children 2 to under 4 years of age | 5 mL (160 mg) every 4 hours Not to exceed 5 doses in a 24-hour period
Children under 2 years of age | Consult a doctor

Other Information

- Each 5 mL contains: sodium 2 mg
- Store at 20° to 25°C (68° to 77°F). [See USP Controlled Room Temperature]
- Keep tightly closed
- Protect from light
- Do not use if foil on cup is missing or torn

Inactive Ingredients

Citric acid, FD&C Red No. 40, flavoring, glycerin, polyethylene glycol, purified water, saccharin sodium, sodium benzoate, sodium citrate, and sorbitol.

Questions Or Comments?

Call (800) 936-3088. You may also report serious side effects to this phone number.

How Supplied

- A red, cherry flavored solution supplied in the following oral dosage cups:

NDC 39328-031-05: | 5 mL unit dose cup
NDC 39328-031-50: | Case contains 50 unit dose cups of 5 mL (39328-031-05).
NDC 39328-031-99: | Case contains 100 unit dose cups of 5 mL (39328-031-05).

NDC 39328-032-10: | 10.15 mL unit dose cup
NDC 39328-032-50: | Case contains 50 unit dose cups of 10.15 mL (39328-032-10).
NDC 39328-032-99: | Case contains 100 unit dose cups of 10.15 mL (39328-032-10).

NDC 39328-034-20: | 20.3 mL unit dose cup
NDC 39328-034-50: | Case contains 50 unit dose cups of 20.3 mL (39328-034-20).
NDC 39328-034-99: | Case contains 100 unit dose cups of 20.3 mL (39328-034-20).

Patrin Pharma
Skokie, IL 60076
www.patrinpharma.com

Rev 02.0424

PRINCIPAL DISPLAY PANEL - 5 mL Cup Label

Delivers 5 mL
NDC 39328-031-05
Acetaminophen
Oral Solution USP
160 mg/5 mL
Alcohol Free
For Institutional Use Only
See Insert

Lot# xxxxxx
Exp: yyyy/mm/dd
Patrin Pharma
Skokie, IL 60076
Rev 03.0324

PRINCIPAL DISPLAY PANEL - 10.15 mL Cup Label

Delivers 10.15 mL
NDC 39328-032-10
Acetaminophen
Oral Solution USP
325 mg/10.15 mL
Alcohol Free
For Institutional Use Only
See Insert

Lot# xxxxxx
Exp: yyyy/mm/dd
Patrin Pharma
Skokie, IL 60076
Rev 03.0324

PRINCIPAL DISPLAY PANEL - 20.3 mL Cup Label

Delivers 20.3 mL
NDC 39328-034-20
Acetaminophen
Oral Solution USP
650 mg/20.3 mL
Alcohol Free
For Institutional Use Only
See Insert

Lot# xxxxxx
Exp: yyyy/mm/dd
Patrin Pharma
Skokie, IL 60076
Rev 03.0324